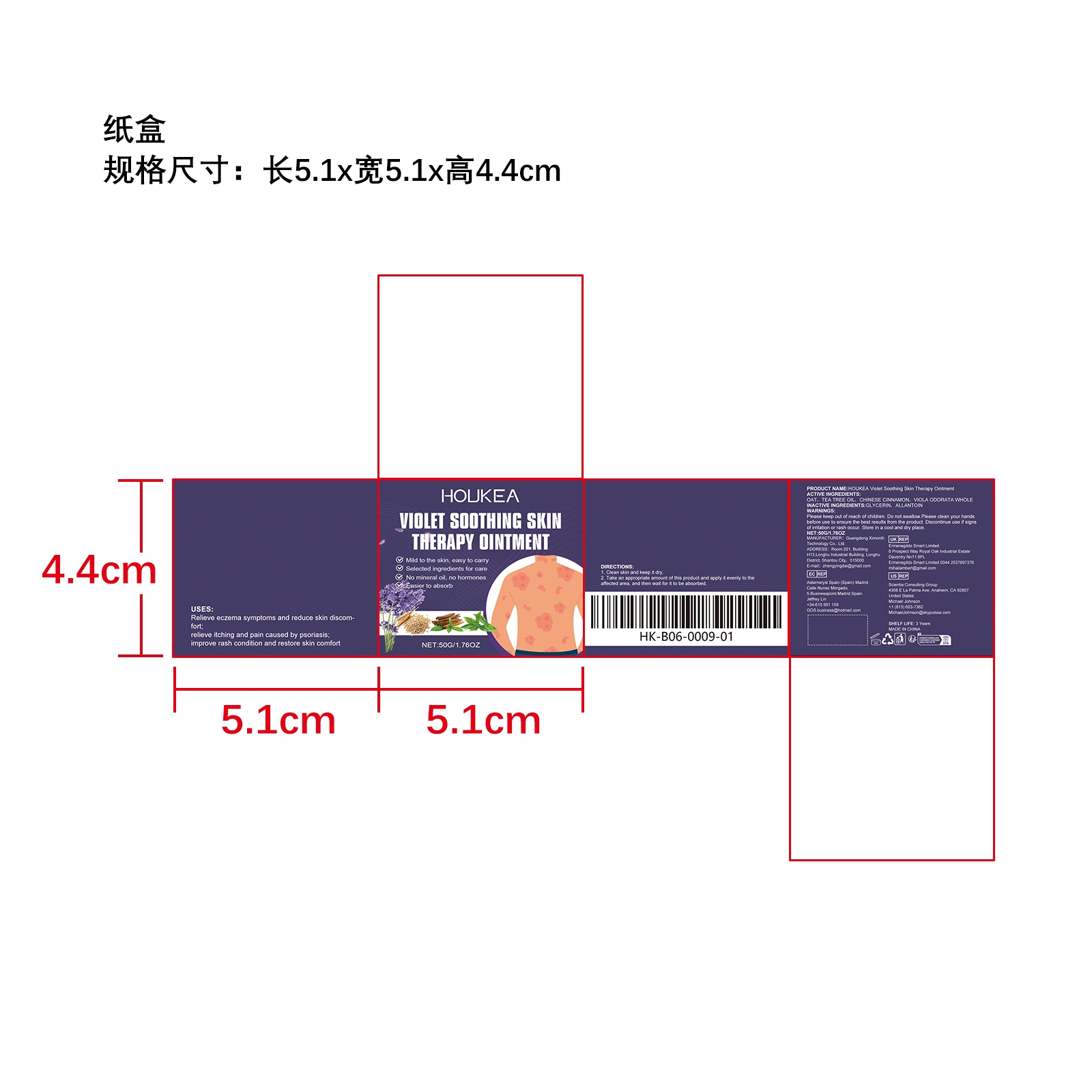 DRUG LABEL: HOUKEA Violet Soothing  Skin Therapy
NDC: 84660-081 | Form: CREAM
Manufacturer: Guangdong Ximonth Technology Co., Ltd.
Category: otc | Type: HUMAN OTC DRUG LABEL
Date: 20241021

ACTIVE INGREDIENTS: CHINESE CINNAMON 5 g/50 g; OAT 7.5 g/50 g; TEA TREE OIL 5 g/50 g; VIOLA ODORATA WHOLE 5 g/50 g
INACTIVE INGREDIENTS: ALLANTOIN 15 g/50 g; GLYCERIN 12.5 g/50 g

Active Ingredient(s)

OAT、TEA TREE OIL、CHINESE CINNAMON、VIOLA ODORATA WHOLE

Purpose

Relieve eczema symptoms and reduce skin discomfort；relieve itching and pain caused by psoriasis；improve rash condition and restore skin comfort

Use

1. Clean skin and keep it dry.

2. Take an appropriate amount of this product and apply it evenly to the affected area, and then waitfor it to be absorbed.

Warnings

Please keep out of reach of children.Do not swallow.Please clean your hands before use to ensure the best results from the product.Discontinue use if signs of irritation or rash occur.Store in a cool and dry place.

STOP USE

Discontinue use if signs of irritation or rash occur.

KEEP OUT OF REACH OF CHILDREN

Please keep out of reach of children. Do not swallow.

STORAGE AND HANDLING

Avoid freezing and excessive heat above 40C (104F) ）
Store in a cool and dry place.

INACTIVE INGREDIENT

GLYCERIN、 ALLANTOIN